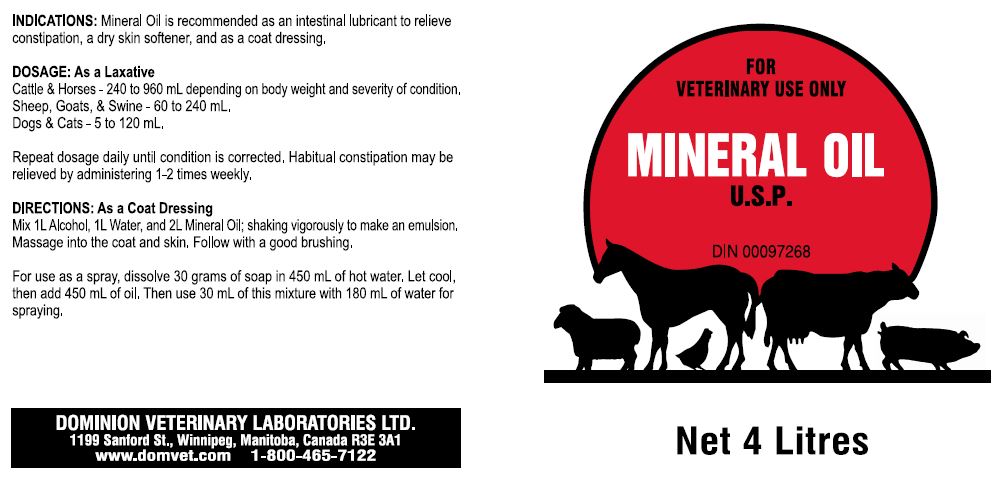 DRUG LABEL: MINERAL
NDC: 64120-106 | Form: OIL
Manufacturer: DOMINION VETERINARY LABORATORIES LTD.
Category: animal | Type: OTC ANIMAL DRUG LABEL
Date: 20211119

ACTIVE INGREDIENTS: MINERAL OIL 100 g/100 mL

DOMINION VETERINARY LABORATORIES - MINERAL OIL USP (64120-106)

INDICATIONS:

MINERAL OIL IS RECOMMENDED AS AN INTESTINAL LUBRICANT TO RELIEVE CONSTIPATION, A DRY SKIN SOFTENER, AND AS A COAT DRESSING.